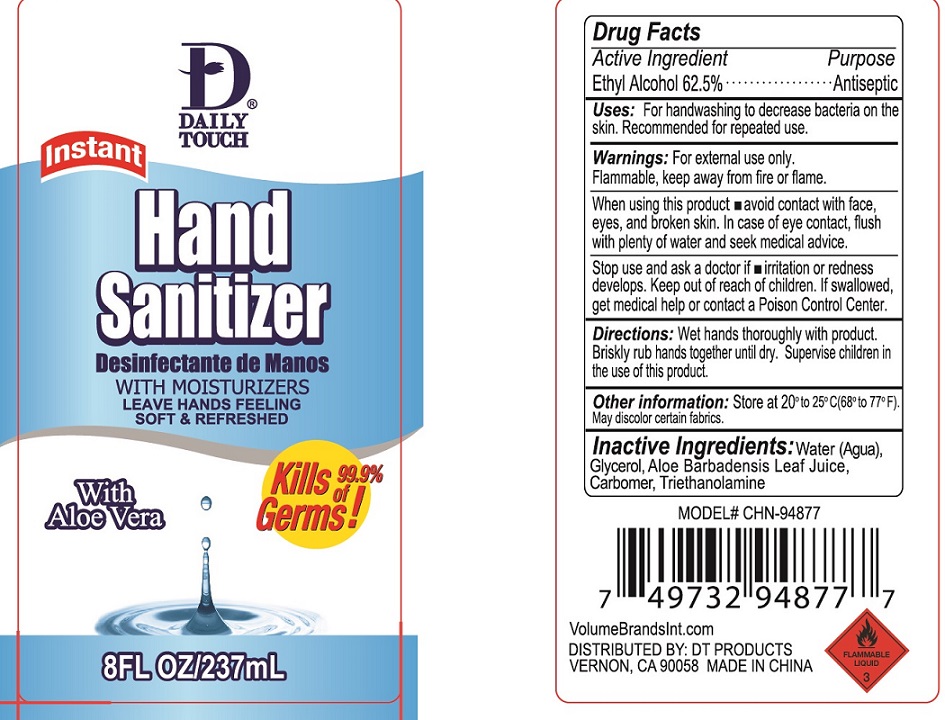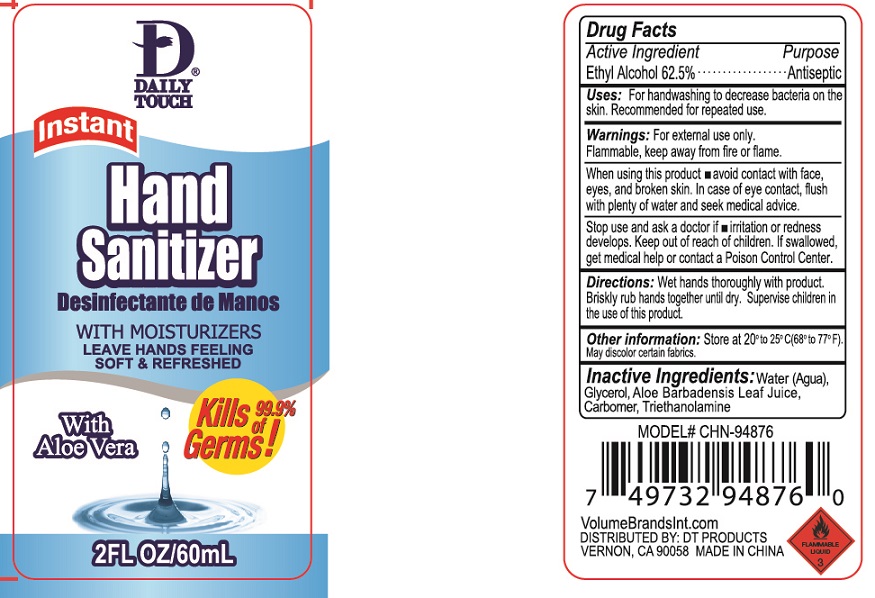 DRUG LABEL: Daily Touch Hand Sanitizer
NDC: 50523-600 | Form: GEL
Manufacturer: Volume Distributors, Inc
Category: otc | Type: HUMAN OTC DRUG LABEL
Date: 20200626

ACTIVE INGREDIENTS: ALCOHOL 0.625 mL/1 mL
INACTIVE INGREDIENTS: WATER; GLYCERIN; ALOE VERA LEAF; CARBOMER HOMOPOLYMER, UNSPECIFIED TYPE; TROLAMINE

Daily Touch Hand Sanitizer

Active Ingredient

Ethyl Alcohol 62.5%

Purpose

Antiseptic

Uses:

For handwashing to decrease bacteria on the skin. Recommended for repeated use.

Warnings:

For external use only. Flammable, kep away from fire or flame.

When using this product

- avoid contact with face, eyes, and broken skin. In case of eye contact, flush with plenty of water and seek medical advice.

Stop use and ask a doctor if

- irritation or redness develops.

Keep out of reach of children.

If swallowed, get medical help or contact a Poison Control Center.

Directions:

Wet hands thoroughly with product. Briskly rub hands together until dry. Supervise children in the use of this product.

Other information:

Store at 20° to 25° C(68° to 77°F).

May discolor certain fabrics.

Inactive Ingredients:

Water (Agua), Glycerol, Aloe Barbadensis Leaf Juice, Carbomer, Triethanolamine